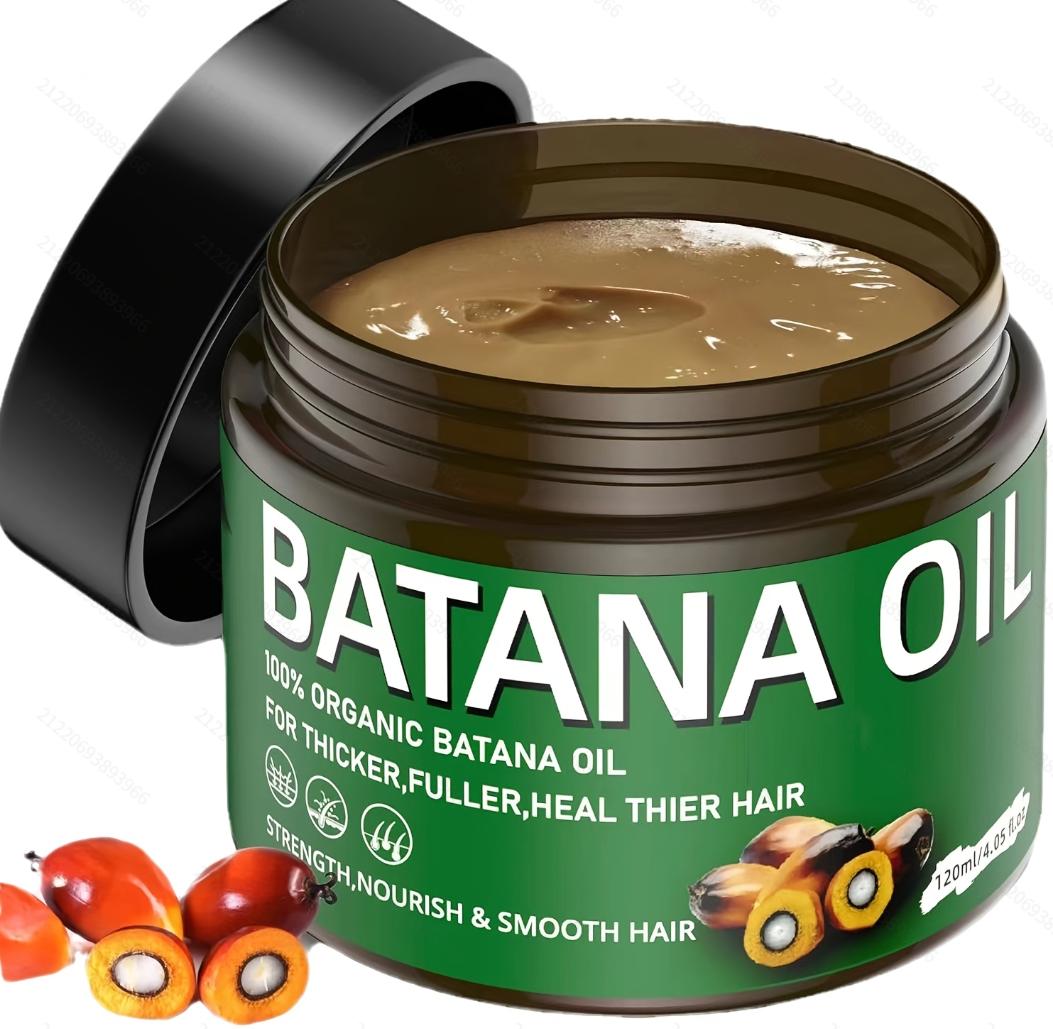 DRUG LABEL: SY1Batana Oil
NDC: 84778-034 | Form: CREAM
Manufacturer: Guangzhou Yixin Cross-border E-commerce Co., Ltd.
Category: otc | Type: HUMAN OTC DRUG LABEL
Date: 20241111

ACTIVE INGREDIENTS: PALM OIL 120 g/120 mL
INACTIVE INGREDIENTS: WATER

COMPONENTS

Batana Oil 120ML

PURPOSE

These healthy fatty acids help nourish hair, strengthen the hair roots, and reduce hair loss and breakage

INDICATIONS AND USAGE

Apply an appropriate amount of Batana Oil to your hair, focusing on the ends or roots, then wrap your hair with a shower cap and leave it on for 30 minutes to an hour, then rinse with warm water.

WARNINGS

For external use only.
If sensitive irritation occurs, please stop using and store in a cool and dry place.

DOSAGE AND ADMINISTRATION

For external use only.

DO NOT USE

Please make sure your skin is clean before use. Avoid using on open wounds or skin with allergic reactions.

WHEN USING

Apply an appropriate amount of Batana Oil on the hair, focusing on the ends or roots of the hair, then wrap the hair with a shower cap, leave it for 30 minutes to 1 hour, and finally wash it with warm water. It is suitable for dry, dull, and dull hair. It can provide deep moisture and restore the softness and luster of the hair.

Do not use on open wounds or allergic skin.

KEEP OUT OF REACH OF CHILDREN

If sxralowed, get medical help or contact a Poison Conirol Cenler ngiht away.

INACTIVE INGREDIENT

water